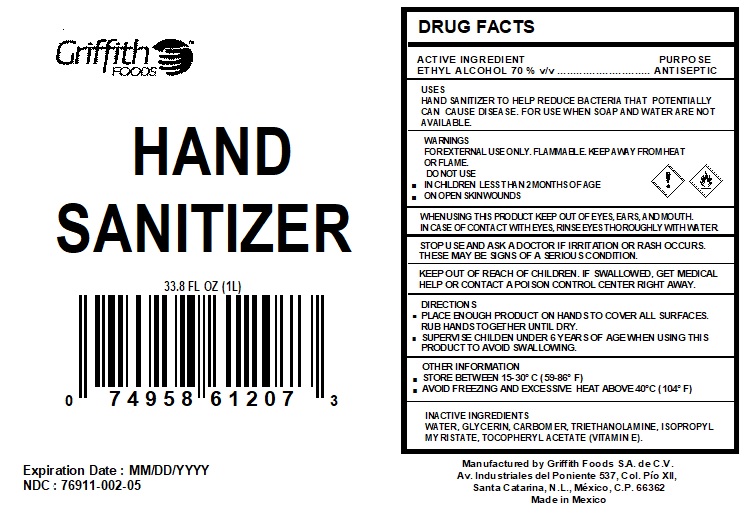 DRUG LABEL: Hand Sanitizer
NDC: 76911-002 | Form: GEL
Manufacturer: Griffith Foods, S.A. de C.V.
Category: otc | Type: HUMAN OTC DRUG LABEL
Date: 20200520

ACTIVE INGREDIENTS: ALCOHOL 70 mL/100 mL
INACTIVE INGREDIENTS: GLYCERIN; CARBOMER 940; WATER; ISOPROPYL MYRISTATE; TROLAMINE; .ALPHA.-TOCOPHEROL

Hand Sanitizer 1L

Active Ingredient(s)

Ethyl Alcohol 70% v/v. Purpose: Antiseptic

Purpose

Antiseptic, Hand Sanitizer

Use

Hand Sanitizer to help reduce bacteria that potentially can cause disease. For use when soap and water are not available.

Warnings

For external use only. Flammable. Keep away from heat or flame

Do not use

- in children less than 2 months of age
- on open skin wounds

When using this product keep out of eyes, ears, and mouth. In case of contact with eyes, rinse eyes thoroughly with water.
Stop use and ask a doctor if irritation or rash occurs. These may be signs of a serious condition.
Keep out of reach of children. If swallowed, get medical help or contact a Poison Control Center right away.

Stop use and ask a doctor if irritation or rash occurs. These may be signs of a serious condition.

Keep out of reach of children. If swallowed, get medical help or contact a Poison Control Center right away.

Directions

Place enough product on hands to cover all surfaces. Rub hands together until dry.

Supervise children under 6 years of age when using this product to avoid swallowing.

Other information

- Store between 15-30°C (59-86°F)
- Avoid freezing and excessive heat above 40°C (104°F)

Inactive ingredients

WATER, GLYCERIN, CARBOMER,TRIETHANOLAMINE, ISOPROPYL MYRISTATE, TOCOPHERYL ACETATE (VITAMIN E).

Package Label - Principal Display Panel

33.8 FL OZ (1L)

1000 mL NDC: 76911-002-05